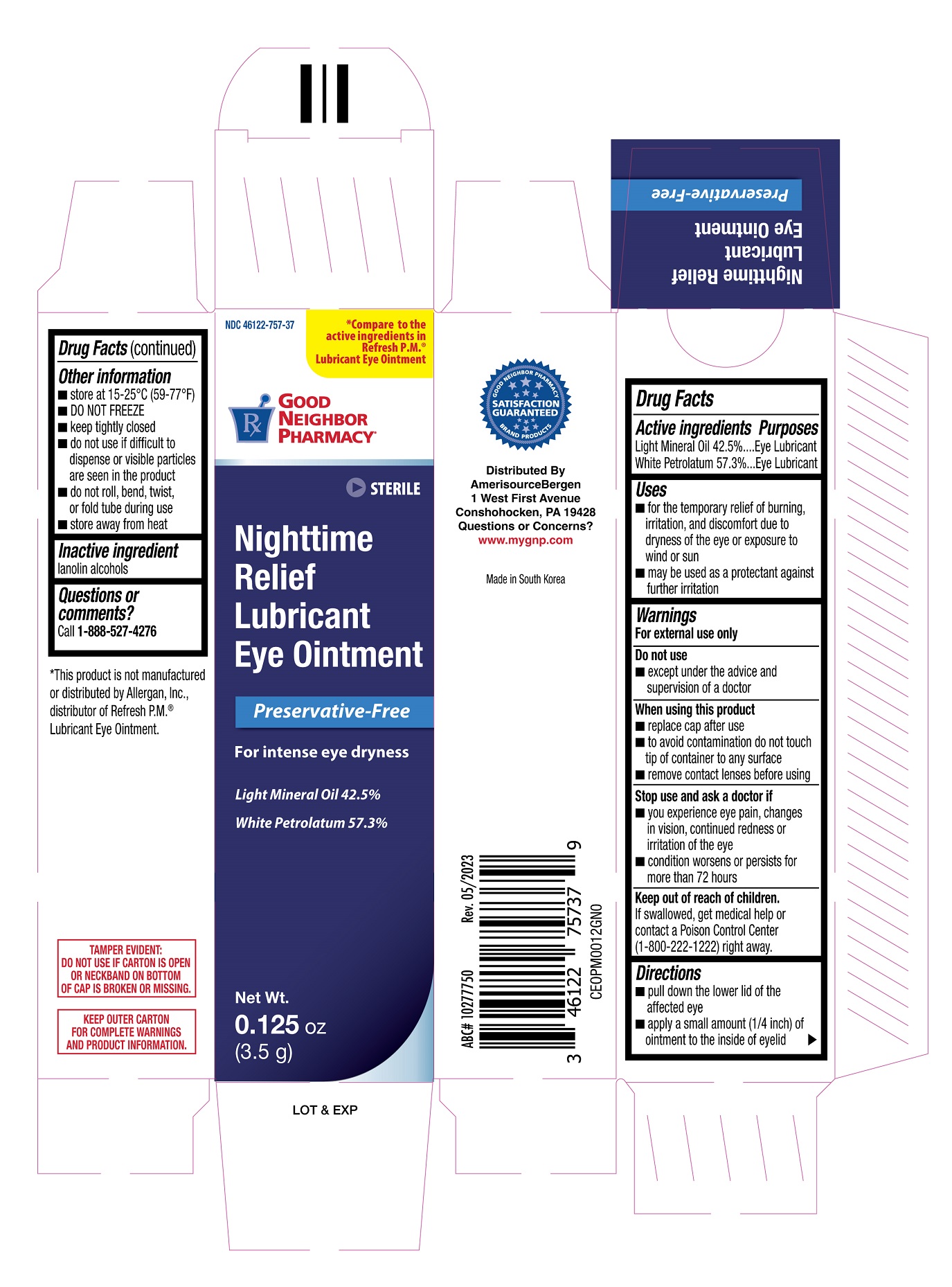 DRUG LABEL: Nighttime Relief Lubricant
NDC: 46122-757 | Form: OINTMENT
Manufacturer: Amerisource Bergen Drug Corp.
Category: otc | Type: HUMAN OTC DRUG LABEL
Date: 20251230

ACTIVE INGREDIENTS: LIGHT MINERAL OIL 425 mg/1 g; WHITE PETROLATUM 573 mg/1 g
INACTIVE INGREDIENTS: LANOLIN ALCOHOLS

GNP Nighttime Relief Lubricant Eye Ointment 3.5g (PLD)

Active ingredients

Light Mineral Oil 42.5%

White Petrolatum 57.3%

Purposes

Eye Lubricant

Eye Lubricant

Uses

- for temporary relief of burning, irritation, and discomfort due to dryness of the eye or exposure to wind or sun
- may be used as a protectant against further irritation

Warnings

For external use only

Do not use

- except under the advice and supervision of a doctor

When using this product

- replace cap after use
- to avoid contamination do not touch tip of container to any surface
- remove contact lenses before using

Stop use and ask a doctor if

- you experience eye pain, changes in vision, continued redness or irritation of the eye
- condition worsens or persists for more than 72 hours

Keep out of reach of children.

If swallowed, get medical help or contact a Poison Control Center (1-800-222-1222) right away.

Directions

- pull down the lower lid of the affected eye
- apply a small amount (1/4 inch) of ointment to the inside of eyelid

Other information

- store at 15-25°C (59-77°F)
- DO NOT FREEZE
- keep tightly closed
- do not use if it is difficult to dispense or visible particles are seen in the product
- do not roll, bend, twist, or fold tube during use
- sore away from heat

Inactive ingredient

lanolin alcohols

Questions or comments?

Call 1-888-527-4276